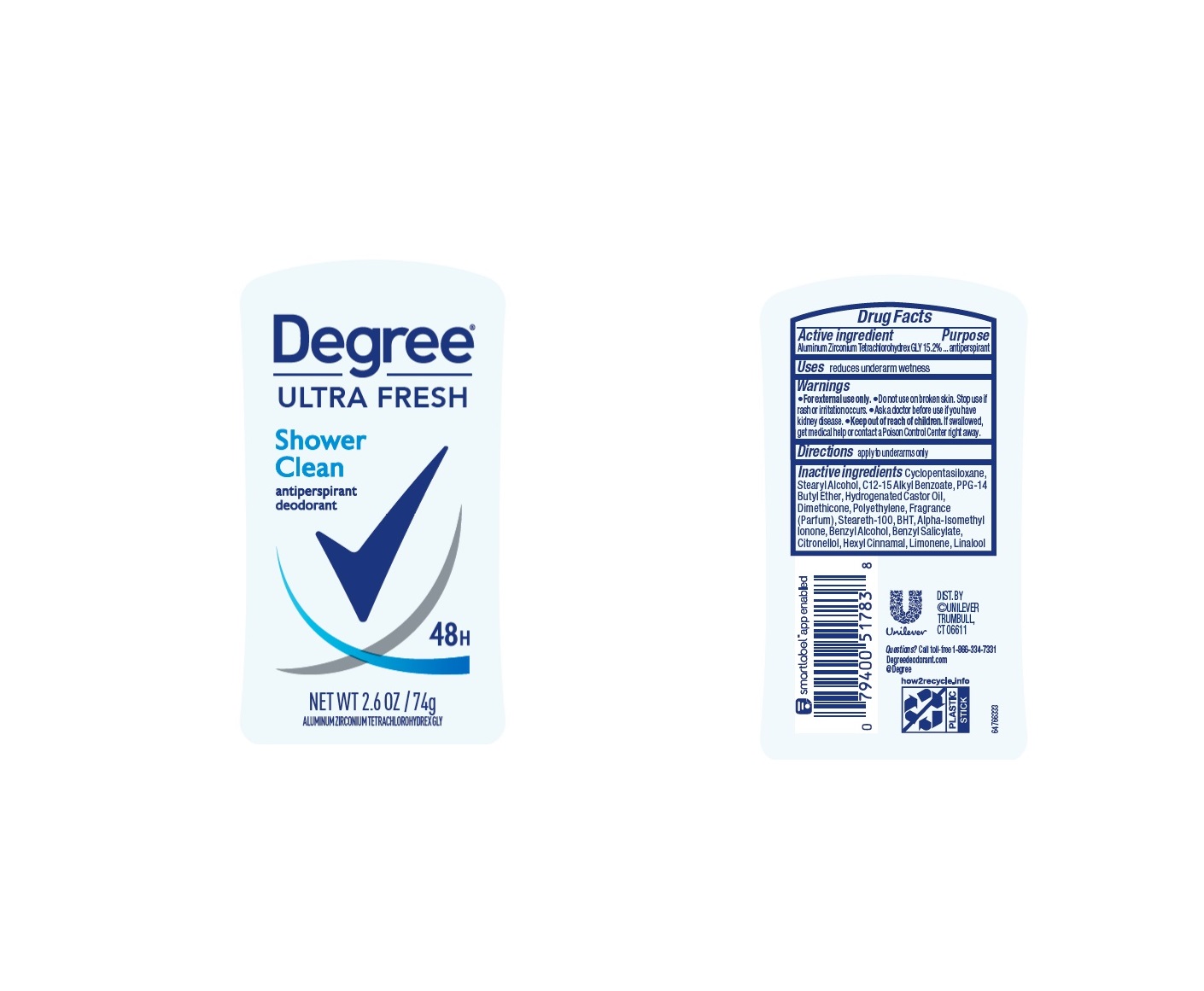 DRUG LABEL: Degree
NDC: 64942-2317 | Form: STICK
Manufacturer: Conopco Inc. d/b/a/ Unilever
Category: otc | Type: HUMAN OTC DRUG LABEL
Date: 20240614

ACTIVE INGREDIENTS: ALUMINUM ZIRCONIUM TETRACHLOROHYDREX GLY 15.2 g/100 g
INACTIVE INGREDIENTS: HIGH DENSITY POLYETHYLENE; LINALOOL, (+/-)-; HYDROGENATED CASTOR OIL; CYCLOMETHICONE 5; BUTYLATED HYDROXYTOLUENE; ALKYL (C12-15) BENZOATE; PPG-14 BUTYL ETHER; STEARYL ALCOHOL; .BETA.-CITRONELLOL, (R)-; BENZYL ALCOHOL; BENZYL SALICYLATE; LIMONENE, (+)-; STEARETH-100; .ALPHA.-HEXYLCINNAMALDEHYDE; ISOMETHYL-.ALPHA.-IONONE; DIMETHICONE

Degree Ultra Fresh Shower Clean 48H Antiperspirant Deodorant

Drug Facts

Active ingredient

Aluminum Zirconium Tetrachlorohydrex GLY (15.2 %)

Purpose

antiperspirant

Uses

reduces underarm wetness

Warnings

• For external use only

• Do not use on broken skin
• Stop use if rash or irritation occurs
• Ask a doctor before use if you have kidney disease

.

• Keep out of reach of children.

If swallowed, get medical help or contact a Poison Control Center right away.

Directions

apply to underarms only

Inactive ingredients

Cyclopentasiloxane, Stearyl Alcohol, C12-15 Alkyl Benzoate, PPG-14 Butyl Ether, Hydrogenated Castor Oil, Dimethicone, Polyethylene, Fragrance (Parfum), Steareth-100, BHT, Alpha-Isomethyl Ionone, Benzyl Alcohol, Benzyl Salicylate, Citronellol, Hexyl Cinnamal, Limonene, Linalool

Questions?

Call toll-free 1-866-334-7331